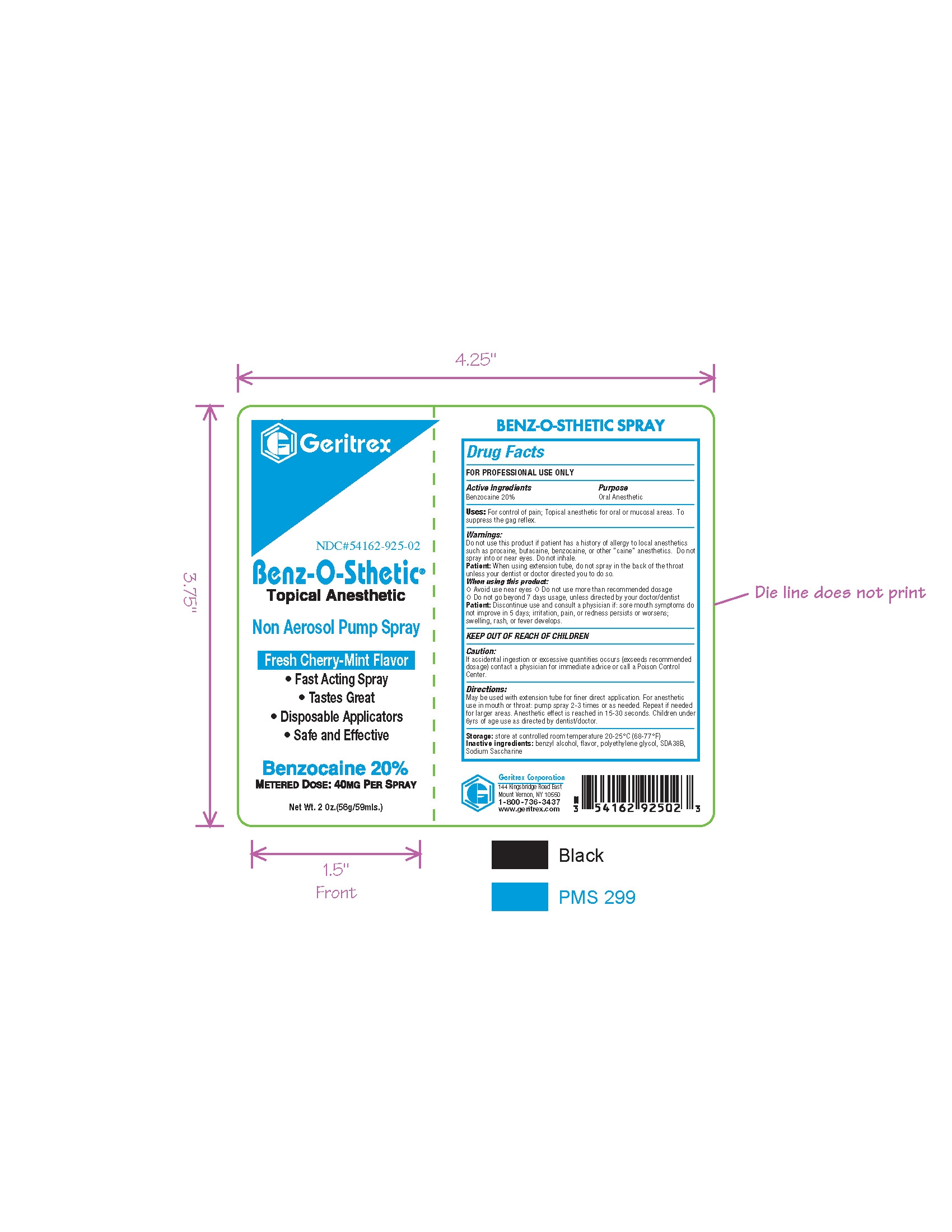 DRUG LABEL: Benz O Sthetic
NDC: 54162-925 | Form: SPRAY
Manufacturer: Geritrex Corp.
Category: otc | Type: HUMAN OTC DRUG LABEL
Date: 20120213

ACTIVE INGREDIENTS: BENZOCAINE 20 mL/100 mL
INACTIVE INGREDIENTS: BENZYL ALCOHOL; POLYETHYLENE GLYCOL 400; N,N-BIS(2-HYDROXYETHYL)-P-PHENYLENEDIAMINE SULFATE; SACCHARIN SODIUM DIHYDRATE

Benz-O-Sthetic Spray

Drugs Facts

Active Ingredients Purpose
Benzocaine 20% Oral Anesthetic

Uses

For control of pain; Topical anesthetic for oral or mucosal areas. To
suppress the gag reflex.

Directions

May be used with extension tube for finer direct application. For anesthetic
use in mouth or throat: pump spray 2-3 times or as needed. Repeat if needed
for larger areas. Anesthetic effect is reached in 15-30 seconds.

DOSAGE AND ADMINISTRATION

Children under 6yrs of age use as directed by dentist/doctor.

Warnings

Do not use this product if patient has a history of allergy to local anesthetics
such as procaine, butacaine, benzocaine, or other “caine” anesthetics. Do not
spray into or near eyes. Do not inhale.
Patient: When using extension tube, do not spray in the back of the throat
unless your dentist or doctor directed you to do so.
When using this product:
Π Avoid use near eyes Π Do not use more than recommended dosage
Π Do not go beyond 7 days usage, unless directed by your doctor/dentist
Patient: Discontinue use and consult a physician if: sore mouth symptoms do
not improve in 5 days; irritation, pain, or redness persists or worsens;
swelling, rash, or fever develops.

Other Ingredients

Benzyl alcohol, flavor, polyethylene glycol, SDA38B,
Sodium Saccharine

Storage

store at controlled room temperature 20-25°C (68-77°F)

Keep out of reach of children

PACKAGE LABEL

Enter section text here